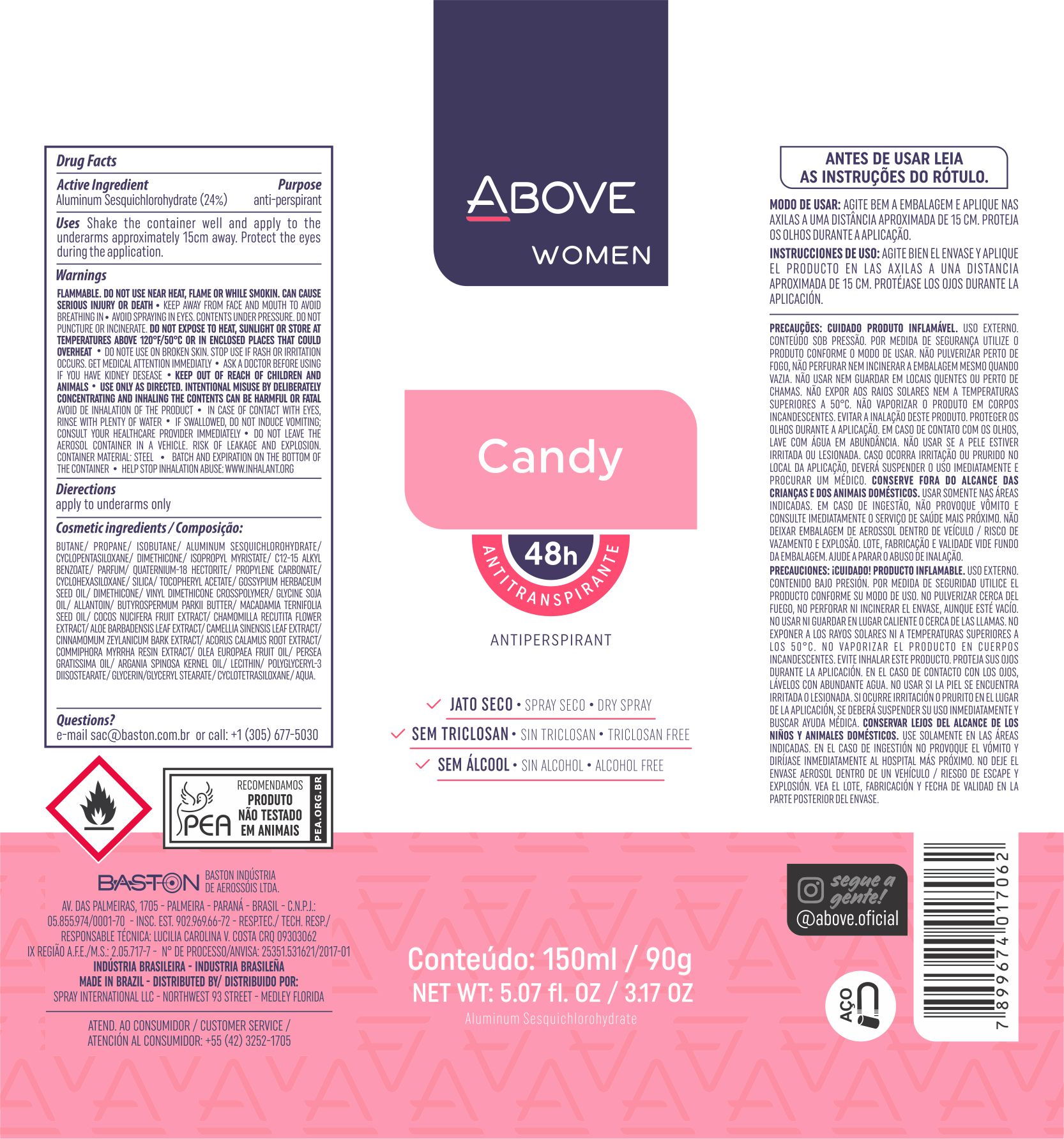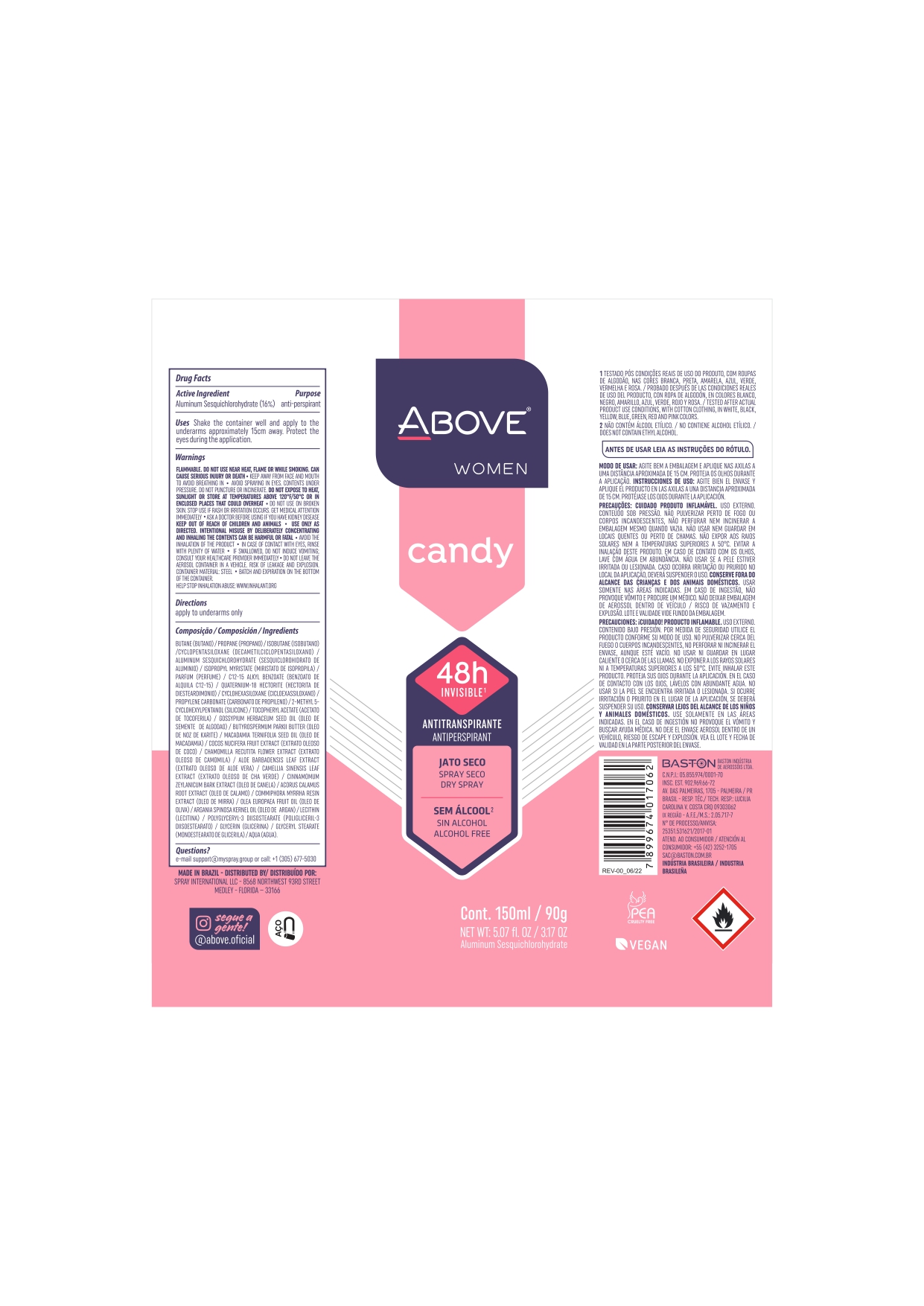 DRUG LABEL: Antiperspirant Above Candy
NDC: 73306-1101 | Form: AEROSOL, SPRAY
Manufacturer: Baston Industria de Aerossóis Ltda
Category: otc | Type: HUMAN OTC DRUG LABEL
Date: 20241009

ACTIVE INGREDIENTS: ALUMINUM SESQUICHLOROHYDRATE 24 g/100 g
INACTIVE INGREDIENTS: .ALPHA.-TOCOPHEROL ACETATE; VINYL DIMETHICONE/METHICONE SILSESQUIOXANE CROSSPOLYMER; DISTEARDIMONIUM HECTORITE; GLYCERYL MONOSTEARATE; WATER; ISOPROPYL MYRISTATE; AVOCADO OIL; GREEN TEA LEAF; CINNAMON BARK OIL; CYCLOMETHICONE 5; MACADAMIA OIL; SHEA BUTTER; ALOE VERA LEAF; PROPYLENE CARBONATE; MYRRH OIL; DIMETHICONE; GLYCERIN; LEVANT COTTON SEED; POLYGLYCERYL-3 DIISOSTEARATE; SILICA DIMETHYL SILYLATE; ACORUS CALAMUS ROOT; ALLANTOIN; BUTANE; CHAMOMILE; ISOBUTANE; PROPANE; ARGAN OIL; COCONUT; LECITHIN, SOYBEAN

Antiperspirant

Uses-reduces underrarm wetness

Uses - reduces underarm wetness

Directions apply to underarms only

Keep Out Of Reach Of Children